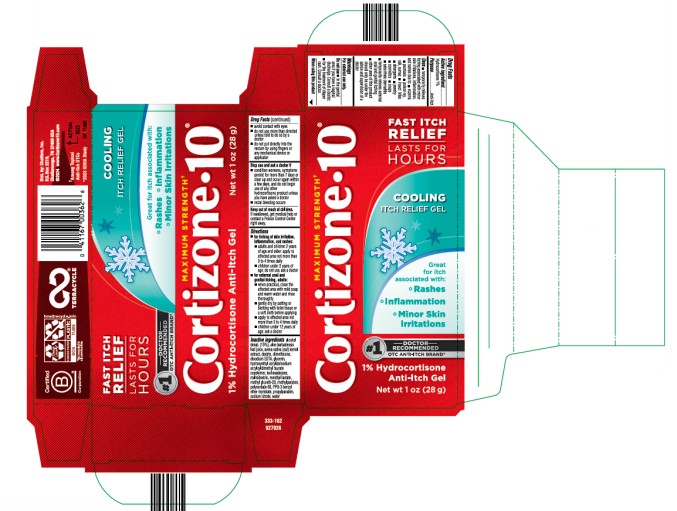 DRUG LABEL: Cortizone 10 Cooling
NDC: 41167-0033 | Form: GEL
Manufacturer: Chattem, Inc.
Category: otc | Type: HUMAN OTC DRUG LABEL
Date: 20250801

ACTIVE INGREDIENTS: HYDROCORTISONE 1 g/100 g
INACTIVE INGREDIENTS: ALCOHOL; ALOE VERA LEAF; OAT; DIMETHICONE; EDETATE DISODIUM ANHYDROUS; GLYCERIN; HYDROXYETHYL ACRYLATE/SODIUM ACRYLOYLDIMETHYL TAURATE COPOLYMER (45000 MPA.S AT 1%); ISOHEXADECANE; MALTODEXTRIN; MENTHYL LACTATE, (-)-; METHYL GLUCETH-20; METHYLPARABEN; POLYSORBATE 60; PPG-3 BENZYL ETHER MYRISTATE; PROPYLPARABEN; SODIUM CITRATE, UNSPECIFIED FORM; WATER

Cortizone 10 Cooling Gel

Cortizone 10
Cooling Gel

Drug Facts

Active ingredient

Hydrocortisone 1%

Purpose

Anti-itch

Uses

■ temporarily relieves itching associated with minor skin irritations, inflammation, and rashes due to:

■ eczema ■ psoriasis ■ poison ivy, oak, sumac ■ insect bites ■ detergents ■ jewelry ■ cosmetics

■ soaps ■ seborrheic dermatitis

■ temporarily relieves external anal and genital itching

■ other uses of this product should only be under the advice and supervision of a doctor

Warnings

For external use only

Do not use

■ in the genital area if you have a vaginal discharge. Consult a doctor. ■ for the treatment of diaper rash. Consult a doctor.

When using this product

■ avoid contact with eyes ■ do not use more than directed unless told to do so by a doctor ■ do not put directly into the rectum by using fingers or any mechanical device or applicator

Stop use and ask a doctor if

■ condition worsens, symptoms persist for more than 7 days or clear up and occur again within a few days, and do not begin use of any other hydrocortisone product unless you have asked a doctor

■ rectal bleeding occurs

Keep out of reach of children.

If swallowed, get medical help or contact a Poison Control Center right away.

Directions

■ for itching of skin irritation, inflammation, and rashes:

■ adults and children 2 years of age and older: apply to affected area not more than 3 to 4 times daily

■ children under 2 years of age: ask a doctor

■ for external anal and genital itching, adults:

■ when practical, clean the affected area with mild soap and warm water and rinse thoroughly

■ gently dry by patting or blotting with toilet tissue or a soft cloth before applying

■ apply to affected area not more than 3 to 4 times daily

■ children under 12 years of age: ask a doctor

Inactive ingredients

alcohol denat. (15%), aloe barbadensis leaf juice, avena sativa (oat) kernel extract, dextrin, dimethicone, disodium EDTA, glycerin, hydroxyethyl acrylate/sodium acryloyldimethyl taurate copolymer, isohexadecane, maltodextrin, menthyl lactate, methyl gluceth-20, methylparaben, polysorbate 60, PPG-3 benzyl ether myristate, propylparaben, sodium citrate, water

PRINCIPAL DISPLAY PANEL

MAXIMUM STRENGTH
Cortizone 10
COOLING
ITCH RELIEF GEL
1% Hydrocortisone
Anti-Itch Gel
Net wt 1 oz (28 g)